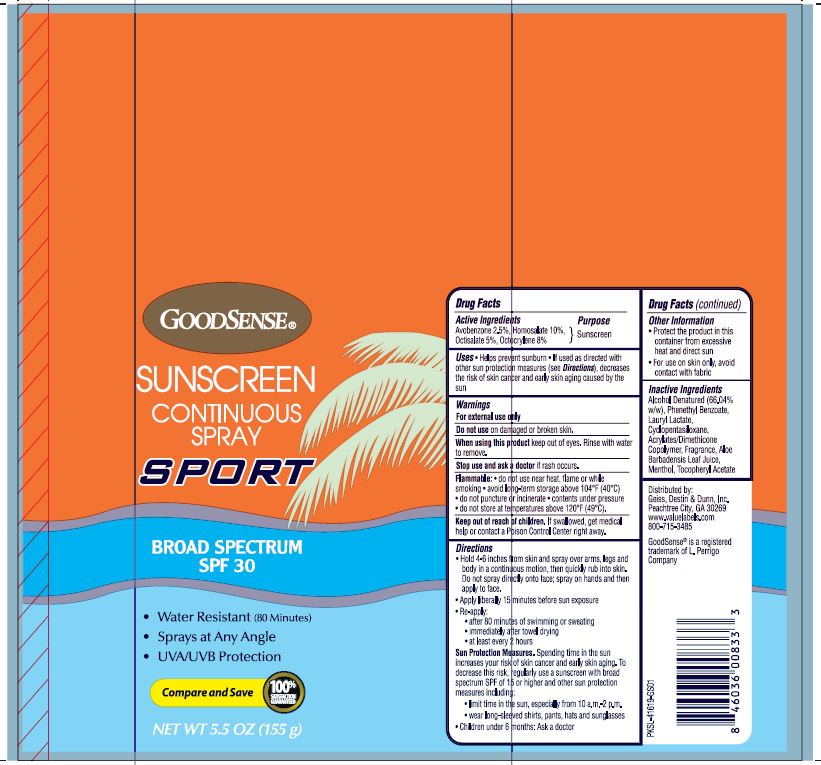 DRUG LABEL: GoodSense SPF 30 Sport CSpray Comfort Can
NDC: 70281-613 | Form: SPRAY
Manufacturer: Solskyn Personal Care LLC
Category: otc | Type: HUMAN OTC DRUG LABEL
Date: 20190807

ACTIVE INGREDIENTS: AVOBENZONE 2.5 g/100 g; HOMOSALATE 10 g/100 g; OCTISALATE 5 g/100 g; OCTOCRYLENE 8 g/100 g
INACTIVE INGREDIENTS: DIMETHICONE CROSSPOLYMER (450000 MPA.S AT 12% IN CYCLOPENTASILOXANE); CYCLOMETHICONE 5; ALOE VERA LEAF; MENTHOL; .ALPHA.-TOCOPHEROL ACETATE; ALCOHOL; PHENETHYL BENZOATE; LAURYL LACTATE

GoodSense SPF 30 Sport CSpray Comfort Can

Active Ingredients

Avobenzone 2.5%

Homosalate 10%

Octisalate 5%

Octocrylene 8%

Purpose

Sunscreen

Uses

- Helps prevent sunburn.
- If used as directed with other sun protection measures (see Directions), decreases the risk of skin cancer and early skin aging caused by the sun

Warnings

For external use only

Do not use on damaged or broken skin.

When using this product keep out of eyes. Rinse with water to remove.

Stop use and ask a doctor if rash occurs.

Flammable

● do not use near heat, flame or while smoking ● avoid long –term storage above 104oF(40oC) ● do not puncture or incinerate ● contents under pressure ● do not store at temperature above 120oF(49oC)

Keep out of reach of children. If swallowed, get medical help or contact a Poison Control Center right away.

Directions

Hold 4-6 inches from skin and spray over arms, legs, and body in a continuous motion, then quickly rub into skin. Do not spray directly onto face; spray on hands and then apply to face.

- Apply liberally 15 minutes before sun exposure

Re-apply:

- after 80- minutes of swimming or sweating
- Immediately after towel drying

- At least every 2 hours

Sun Protection Measures. Spending time in the sun increases your risk of skin cancer and early skin aging. To decrease this risk, regularly use a sunscreen with ·

- Limit time in the sun, especially from 10a.m.-2 p.m.
- Wear long-sleeved shirts, pants, hats, and sunglasses.
- Children under 6 months: Ask a doctor.

Other Information

Protect the product in this container from excessive heat and direct sun

For use on skin only, avoid contact with fabric

Inactive Ingredients

Alcohol Denatured (66.04% w/w), Phenethyl Benzoate, Lauryl Lactate, Cyclopentasiloxane, Acrylates/Dimethicone Copolymer, Fragrance, Aloe Barbadensis Leaf Juice, Menthol, Tocopheryl Acetate

Questions

Distributed by:

Geiss, Destin & Dunn, Inc.

Peach tree City, GA 30269

www.valuelabels.com

800-715-3485

GoodSense® is a registered trademark of L. Perrigo Company

Principal Display Panel

GOODSENSE®

SUNSCREEN

CONTINUOUS

SPRAY

SPORT

BROAD SPECTRUM

SPF 30

Water Resistant (80 Minutes)
Spray at Any Angle
UVA/UVB Protection

*Compare and Save 100% Satisfaction Guaranteed

NET WT 5.5 OZ (155 g)